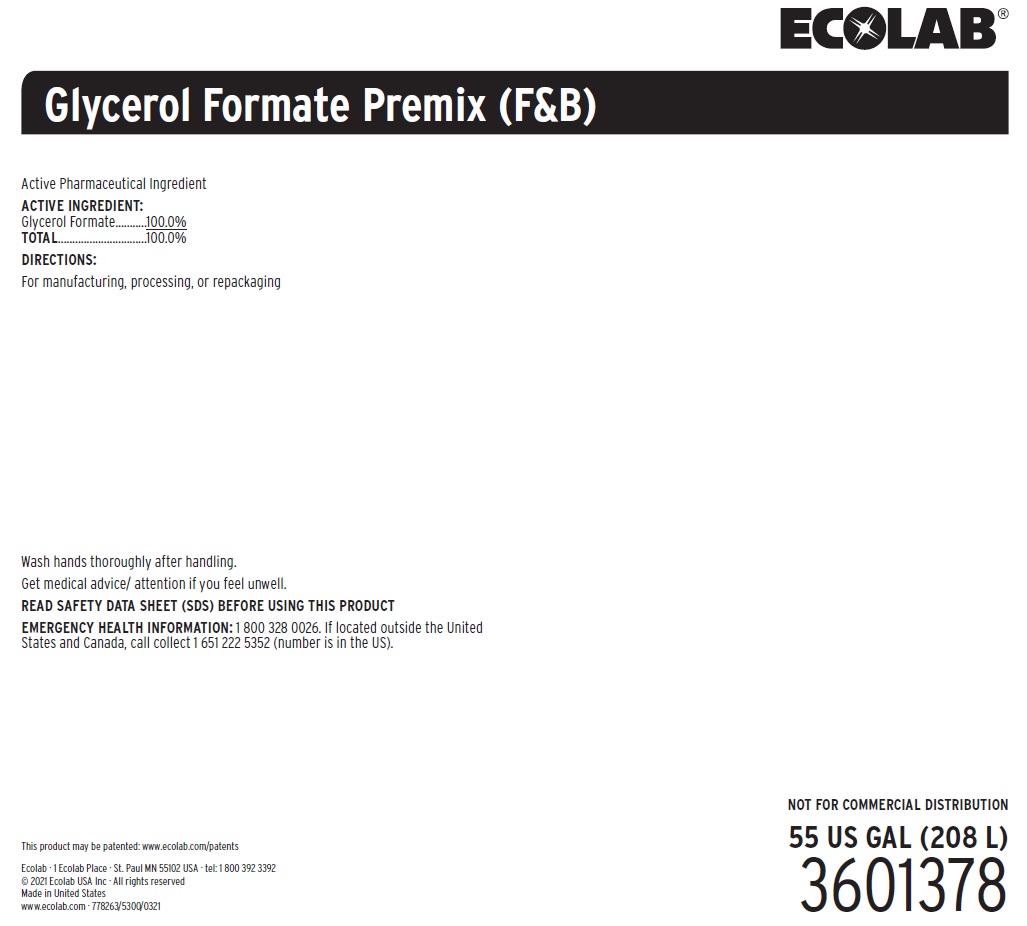 DRUG LABEL: Glycerol Formate Premix
NDC: 47593-641 | Form: SOLUTION
Manufacturer: Ecolab Inc.
Category: other | Type: BULK INGREDIENT - ANIMAL DRUG
Date: 20250123

ACTIVE INGREDIENTS: GLYCERYL DI AND TRIFORMATE 1000 mg/1 mL

Wash hands thoroughly after handling.

Get medical advice/attention if you feel unwell.

VETERINARY INDICATIONS

Active Pharmaceutical Ingredient

OTHER SAFETY INFORMATION

READ SAFETY DATA SHEET (SDS) BEFORE USING THIS PRODUCT

EMERGENCY HEALTH INFORMATION: 1 800 328 0026. If located outside the United States and Canada, call collect 1 651 222 5352 (number is in the US).

Representative label and principal display panel

ECOLAB

Glycerol Formate Premix (F&B)

Active Pharmaceutical Ingredient

ACTIVE INGREDIENT:

Glycerol Formate...........100.0%

TOTAL...............................100.0%

DIRECTIONS:

For manufacturing, processing, or repackaging

NOT FOR COMMERCIAL DISTRIBUTION

55 US GAL (208 L)

3601378

This product may be patented: www.ecolab.com/patents

Ecolab · 1 Ecolab Place · St. Paul MN 55102 USA · tel: 1 800 392 3392 © 2021 Ecolab USA Inc · All rights reserved

Made in United States

www.ecolab.com · 778263/5300/0321